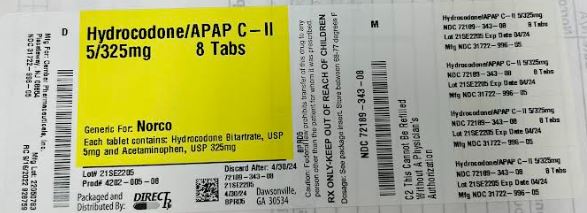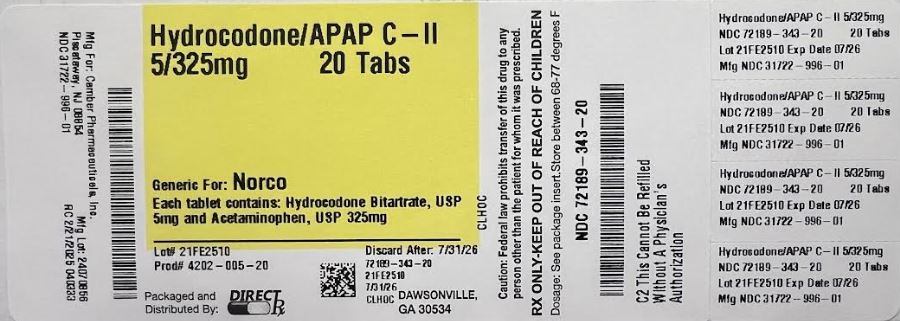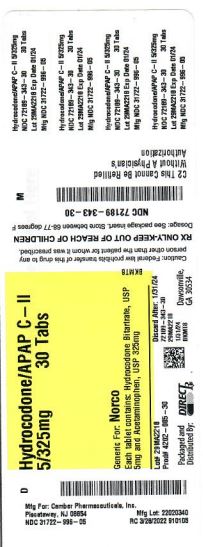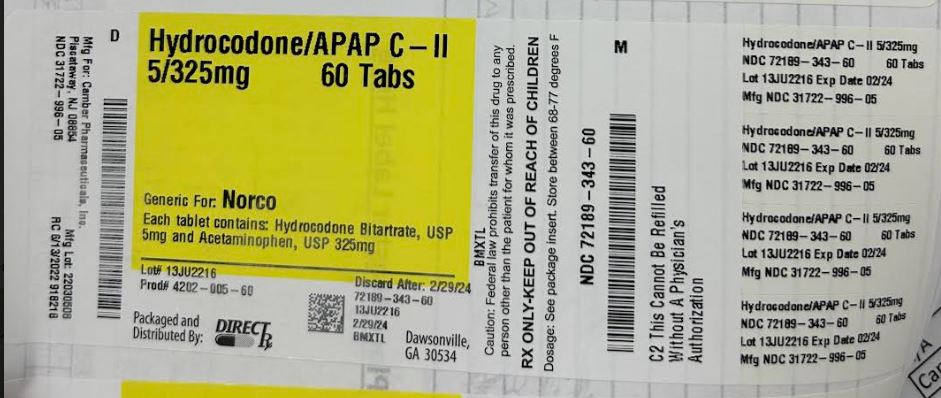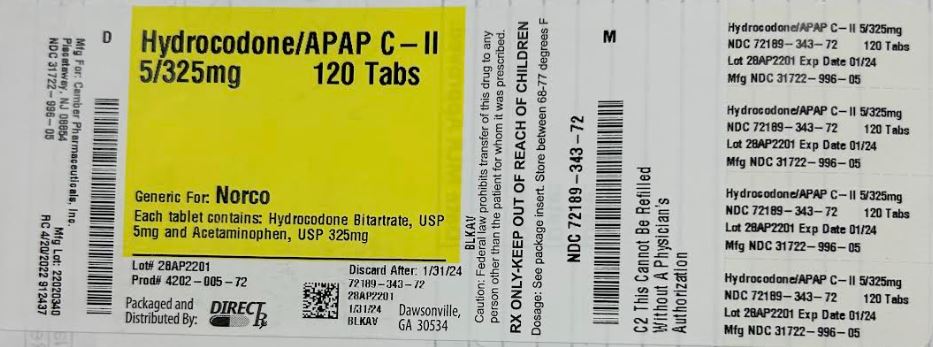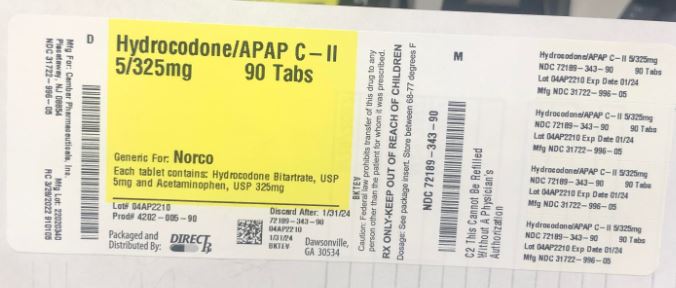 DRUG LABEL: HYDROCODONE BITARTRATE AND ACETAMINOPHEN
NDC: 72189-343 | Form: TABLET
Manufacturer: Direct Rx
Category: prescription | Type: HUMAN PRESCRIPTION DRUG LABEL
Date: 20250221
DEA Schedule: CII

ACTIVE INGREDIENTS: HYDROCODONE BITARTRATE 5 mg/1 1; ACETAMINOPHEN 325 mg/1 1
INACTIVE INGREDIENTS: STEARIC ACID; STARCH, CORN; CROSPOVIDONE; POVIDONE; CELLULOSE, MICROCRYSTALLINE; SILICON DIOXIDE

HYDROCODONE BITARTRATE AND ACETAMINOPHEN

DESCRIPTION

Hydrocodone bitartrate and acetaminophen, USP is available in tablet form for oral administration.
Hydrocodone bitartrate is an opioid analgesic and occurs as fine, white crystals or as a crystalline powder. It is affected by light. The chemical name is 4,5α-epoxy-3-methoxy-17-methylmorphinan-6-one tartrate (1:1) hydrate (2:5). It has the following structural formula:
Hydrocodone Bitartrate- Struct
Acetaminophen, 4' -hydroxyacetanilide, a slightly bitter, white, odorless, crystalline powder, is a non-opiate, non-salicylate analgesic and antipyretic. It has the following structural formula:
Acetaminophen- Struct
Each Hydrocodone Bitartrate and Acetaminophen Tablet, USP contains:
Strength Hydrocodone Bitartrate Acetaminophen
5 mg/325 mg 5 mg 325 mg
10 mg/325 mg 10 mg 325 mg
In addition, each tablet contains the following inactive ingredients: microcrystalline cellulose, corn starch, colloidal silicon dioxide, crospovidone, pregelatinized starch, povidone, and stearic acid.
Hydrocodone Bitartrate and Acetaminophen Tablets, USP complies to USP Dissolution Test 1.

CLINICAL PHARMACOLOGY

Mechanism of Action

Hydrocodone is a full opioid agonist with relative selectivity for the mu-opioid (μ) receptor, although it can interact with other opioid receptors at higher doses. The principal therapeutic action of hydrocodone is analgesia. Like all full opioid agonists, there is no ceiling effect for analgesia with hydrocodone. Clinically, dosage is titrated to provide adequate analgesia and may be limited by adverse reactions, including respiratory and CNS depression.

The precise mechanism of the analgesic action is unknown. However, specific CNS opioid receptors for endogenous compounds with opioid-like activity have been identified throughout the brain and spinal cord and are thought to play a role in the analgesic effects of this drug. The precise mechanism of the analgesic properties of acetaminophen is not established but is thought to involve central actions.

Pharmacodynamics

Effects on the Central Nervous System

The principal therapeutic action of hydrocodone is analgesia. Hydrocodone produces respiratory depression by direct action on brain stem respiratory centers. The respiratory depression involves a reduction in the responsiveness of the brain stem respiratory centers to both increases in carbon dioxide tension and electrical stimulation.

Hydrocodone causes miosis, even in total darkness. Pinpoint pupils are a sign of opioid overdose but are not pathognomonic (e.g., pontine lesions of hemorrhagic or ischemic origins may produce similar findings). Marked mydriasis rather than miosis may be seen due to hypoxia in overdose situations.

Therapeutic doses of acetaminophen have negligible effects on the cardiovascular or respiratory systems; however, toxic doses may cause circulatory failure and rapid, shallow breathing.

Effects on the Gastrointestinal Tract and Other Smooth Muscle

Hydrocodone causes a reduction in motility associated with an increase in smooth muscle tone in the antrum of the stomach and duodenum. Digestion of food in the small intestine is delayed and propulsive contractions are decreased. Propulsive peristaltic waves in the colon are decreased, while tone may be increased to the point of spasm, resulting in constipation. Other opioid-induced effects may include a reduction in biliary and pancreatic secretions, spasm of sphincter of Oddi, and transient elevations in serum amylase.

Effects on the Cardiovascular System

Hydrocodone produces peripheral vasodilation which may result in orthostatic hypotension or syncope. Manifestations of histamine release and/or peripheral vasodilation may include pruritus, flushing, red eyes, sweating, and/or orthostatic hypotension.

Effects on the Endocrine System

Opioids inhibit the secretion of adrenocorticotropic hormone (ACTH), cortisol, and luteinizing hormone (LH) in humans [see ADVERSE REACTIONS]. They also stimulate prolactin, growth hormone (GH) secretion, and pancreatic secretion of insulin and glucagon.

Chronic use of opioids may influence the hypothalamic-pituitary-gonadal axis, leading to androgen deficiency that may manifest as symptoms as low libido, impotence, erectile dysfunction, amenorrhea, or infertility. The causal role of opioids in the syndrome of hypogonadism is unknown because the various medical, physical, lifestyle, and psychological stressors that may influence gonadal hormone levels have not been adequately controlled for in studies conducted to date [see ADVERSE REACTIONS].

Effects on the Immune System

Opioids have been shown to have a variety of effects on components of the immune system. The clinical significance of these findings is unknown. Overall, the effects of opioids appear to be modestly immunosuppressive.

Concentration-Efficacy Relationships

The minimum effective analgesic concentration will vary widely among patients, especially among patients who have been previously treated with potent agonist opioids. The minimum effective analgesic concentration of hydrocodone for any individual patient may increase over time due to an increase in pain, the development of a new pain syndrome, and/or the development of analgesic tolerance [see DOSAGE AND ADMINISTRATION].

Concentration-Adverse Reaction Relationships

There is a relationship between increasing hydrocodone plasma concentration and increasing frequency of dose-related opioid adverse reactions such as nausea, vomiting, CNS effects, and respiratory depression. In opioid-tolerant patients, the situation may be altered by the development of tolerance to opioid-related adverse reactions [see DOSAGE AND ADMINISTRATION].

Pharmacokinetics

The behavior of the individual components is described below.

Hydrocodone

Following a 10 mg oral dose of hydrocodone administered to five adult male subjects, the mean peak concentration was 23.6 ± 5.2 ng/mL. Maximum serum levels were achieved at 1.3 ± 0.3 hours and the half-life was determined to be 3.8 ± 0.3 hours.

Hydrocodone exhibits a complex pattern of metabolism including O-demethylation, N-demethylation and 6-keto reduction to the corresponding 6-α- and 6-β-hydroxymetabolites. See OVERDOSAGE for toxicity information.

CYP3A4 mediated N-demethylation to norhydrocodone is the primary metabolic pathway of hydrocodone with a lower contribution from CYP2D6 mediated O-demethylation to hydromorphone. Hydromorphone is formed from the O-demethylation of hydrocodone and may contribute to the total analgesic effect of hydrocodone. Therefore, the formation of these and related metabolites can, in theory, be affected by other drugs [see PRECAUTIONS; Drug Interactions]. N-demethylation of hydrocodone to form norhydrocodone via CYP3A4 while O-demethylation of hydrocodone to hydromorphone is predominantly catalyzed by CYP2D6 and to a lesser extent by an unknown low affinity CYP enzyme. Hydrocodone and its metabolites are eliminated primarily in the kidneys.

Acetaminophen

Acetaminophen is rapidly absorbed from the gastrointestinal tract and is distributed throughout most body tissues. A small fraction (10-25%) of acetaminophen is bound to plasma proteins. The plasma half-life is 1.25 to 3 hours, but may be increased by liver damage and following overdosage. Elimination of acetaminophen is principally by liver metabolism (conjugation) and subsequent renal excretion of metabolites. Acetaminophen is primarily metabolized in the liver by first-order kinetics and involves three principal separate pathways: conjugation with glucuronide; conjugation with sulfate; and oxidation via the cytochrome, P450-dependent, mixed-function oxidase enzyme pathway to form a reactive intermediate metabolite, which conjugates with glutathione and is then further metabolized to form cysteine and mercapturic acid conjugates. The principal cytochrome P450 isoenzyme involved appears to be CYP2E1, with CYP1A2 and CYP3A4 as additional pathways. Approximately 85% of an oral dose appears in the urine within 24 hours of administration, most as the glucuronide conjugate, with small amounts of other conjugates and unchanged drug.

See OVERDOSAGE for toxicity information.

INDICATIONS AND USAGE

Hydrocodone bitartrate and acetaminophen tablets, USP are indicated for the management of pain severe enough to require an opioid analgesic and for which alternative treatments are inadequate.

Limitations of Use

Because of the risks of addiction, abuse, and misuse, with opioids, even at recommended doses [see WARNINGS], reserve hydrocodone bitartrate and acetaminophen tablets, USP for use in patients for whom alternative treatment options (e.g., non-opioid analgesics):

have not been tolerated, or are not expected to be tolerated,
have not provided adequate analgesia, or are not expected to provide adequate analgesia

ADVERSE REACTIONS

The following adverse reactions have been identified during post approval use of hydrocodone and acetaminophen tablets. Because these reactions are reported voluntarily from a population of uncertain size, it is not always possible to reliably estimate their frequency or establish a causal relationship to drug exposure.

The most frequently reported adverse reactions are light-headedness, dizziness, sedation, nausea and vomiting.

Other adverse reactions include:

Central Nervous System: Drowsiness, mental clouding, lethargy, impairment of mental and physical performance, anxiety, fear, dysphoria, psychological dependence, mood changes.

Gastrointestinal System: Constipation.

Genitourinary System: Ureteral spasm, spasm of vesical sphincters, and urinary retention.

Special Senses: Cases of hearing impairment or permanent loss have been reported predominately in patients with chronic overdose.

Dermatological: Skin rash, pruritus, Stevens-Johnson syndrome, toxic epidermal necrolysis, allergic reactions.

Hematological: Thrombocytopenia, agranulocytosis.

Serotonin syndrome: Cases of serotonin syndrome, a potentially life-threatening condition, have been reported during concomitant use of opioids with serotonergic drugs.
Adrenal insufficiency: Cases of adrenal insufficiency have been reported with opioid use, more often following greater than one month of use.
Anaphylaxis: Anaphylaxis has been reported with ingredients contained in hydrocodone bitartrate and acetaminophen tablets.
Androgen deficiency: Cases of androgen deficiency have occurred with chronic use of opioids [see CLINICAL PHARMACOLOGY].

DRUG ABUSE AND DEPENDENCE

Controlled Substance

Hydrocodone bitartrate and acetaminophen tablets contain hydrocodone, a Schedule II controlled substance.

Abuse

Hydrocodone bitartrate and acetaminophen tablets contain hydrocodone, a substance with a high potential for abuse similar to other opioids, including fentanyl, hydrocodone, hydromorphone, methadone, morphine, oxycodone, oxymorphone, and tapentadol, can be abused and are subject to misuse, addiction, and criminal diversion [see WARNINGS].

All patients treated with opioids require careful monitoring for signs of abuse and addiction, because use of opioid analgesic products carries the risk of addiction even under appropriate medical use.

Prescription drug abuse is the intentional non-therapeutic use of a prescription drug, even once, for its rewarding psychological or physiological effects.

Drug addiction is a cluster of behavioral, cognitive, and physiological phenomena that develop after repeated substance use and includes a strong desire to take the drug, difficulties in controlling its use, persisting in its use despite harmful consequences, a higher priority given to drug use than to other activities and obligations, increased tolerance, and sometimes a physical withdrawal.

“Drug-seeking” behavior is very common in persons with substance use disorders. Drug-seeking tactics include emergency calls or visits near the end of office hours, refusal to undergo appropriate examination, testing, or referral, repeated “loss” of prescriptions, tampering with prescriptions and reluctance to provide prior medical records or contact information for other treating healthcare provider(s). “Doctor shopping” (visiting multiple prescribers to obtain additional prescriptions) is common among drug abusers and people suffering from untreated addiction. Preoccupation with achieving adequate pain relief can be appropriate behavior in a patient with poor pain control.

Abuse and addiction are separate and distinct from physical dependence and tolerance. Healthcare providers should be aware that addiction may not be accompanied by concurrent tolerance and symptoms of physical dependence in all addicts. In addition, abuse of opioids can occur in the absence of true addiction.

Hydrocodone bitartrate and acetaminophen tablets, like other opioids, can be diverted for non-medical use into illicit channels of distribution. Careful record-keeping of prescribing information, including quantity, frequency, and renewal requests, as required by state and federal law, is strongly advised.

Proper assessment of the patient, proper prescribing practices, periodic re-evaluation of therapy, and proper dispensing and storage are appropriate measures that help to limit abuse of opioid drugs.

Risks Specific to Abuse of Hydrocodone Bitartrate and Acetaminophen Tablets

Hydrocodone bitartrate and acetaminophen tablets are for oral use only. Hydrocodone bitartrate and acetaminophen tablets pose a risk of overdose and death. The risk is increased with concurrent abuse of hydrocodone bitartrate and acetaminophen tablets with alcohol and other central nervous system depressants.

Parenteral drug abuse is commonly associated with transmission of infectious diseases such as hepatitis and HIV.

Dependence

Both tolerance and physical dependence can develop during chronic opioid therapy. Tolerance is the need for increasing doses of opioids to maintain a defined effect such as analgesia (in the absence of disease progression or other external factors). Tolerance may occur to both the desired and undesired effects of drugs, and may develop at different rates for different effects.

Physical dependence is a physiological state in which the body adapts to the drug after a period of regular exposure, resulting in withdrawal symptoms after abrupt discontinuation or a significant dosage reduction of a drug. Withdrawal also may be precipitated through the administration of drugs with opioid antagonist activity (e.g., naloxone, nalmefene), mixed agonist/antagonist analgesics (e.g., pentazocine, butorphanol, nalbuphine), or partial agonists (e.g., buprenorphine). Physical dependence may not occur to a clinically significant degree until after several days to weeks of continued opioid usage.

Do not abruptly discontinue hydrocodone bitartrate and acetaminophen tablets in a patient physically dependent on opioids. Rapid tapering of hydrocodone bitartrate and acetaminophen tablets in a patient physically dependent on opioids may lead to serious withdrawal symptoms, uncontrolled pain, and suicide. Rapid discontinuation has also been associated with attempts to find other sources of opioid analgesics, which may be confused with drug-seeking for abuse.

When discontinuing hydrocodone bitartrate and acetaminophen tablets, gradually taper the dosage using a patient specific plan that considers the following: the dose of hydrocodone bitartrate and acetaminophen tablets the patient has been taking, the duration of treatment, and the physical and psychological attributes of the patient. To improve the likelihood of a successful taper and minimize withdrawal symptoms, it is important that the opioid tapering schedule is agreed upon by the patient. In patients taking opioids for a long duration at high doses, ensure that a multimodal approach to pain management, including mental health support (if needed), is in place prior to initiating an opioid analgesic taper [see DOSAGE AND ADMINISTRATION, WARNINGS].

Infants born to mothers physically dependent on opioids will also be physically dependent and may exhibit respiratory difficulties and withdrawal signs [see PRECAUTIONS; Pregnancy].

OVERDOSAGE

Following an acute overdosage, toxicity may result from hydrocodone or acetaminophen.

Clinical Presentation

Acute overdosage with hydrocodone bitartrate and acetaminophen tablets can be manifested by respiratory depression, somnolence progressing to stupor or coma, skeletal muscle flaccidity, cold and clammy skin, constricted pupils, and, in some cases, pulmonary edema, bradycardia, hypotension, partial or complete airway obstruction, atypical snoring, and death. Marked mydriasis rather than miosis may be seen with hypoxia in overdose situations.

Acetaminophen

Dose-dependent, potentially fatal hepatic necrosis is the most serious adverse effect of acetaminophen overdosage. Renal tubular necrosis, hypoglycemic coma and coagulation defects may also occur.

Early symptoms following a potentially hepatotoxic overdose may include: nausea, vomiting, diaphoresis and general malaise. Clinical and laboratory evidence of hepatic toxicity may not be apparent until 48 to 72 hours post-ingestion.

Treatment of Overdose

Hydrocodone

In case of overdose, priorities are the re-establishment of a patent and protected airway and institution of assisted or controlled ventilation, if needed. Employ other supportive measures (including oxygen and vasopressors) in the management of circulatory shock and pulmonary edema as indicated. Cardiac arrest or arrhythmias will require advanced life-support techniques.

Opioid antagonists, such as naloxone, are specific antidotes to respiratory depression resulting from opioid overdose. For clinically significant respiratory or circulatory depression secondary to opioid overdose, administer an opioid antagonist.

Because the duration of opioid reversal is expected to be less than the duration of action of hydrocodone in hydrocodone bitartrate and acetaminophen tablets, carefully monitor the patient until spontaneous respiration is reliably reestablished. If the response to an opioid antagonist is suboptimal or only brief in nature, administer additional antagonist as directed by the product’s prescribing information.

In an individual physically dependent on opioids, administration of the recommended usual dosage of the antagonist will precipitate an acute withdrawal syndrome. The severity of the withdrawal symptoms experienced will depend on the degree of physical dependence and the dose of the antagonist administered. If a decision is made to treat serious respiratory depression in the physically dependent patient, administration of the antagonist should be initiated with care and by titration with smaller than usual doses of the antagonist.

Acetaminophen

Gastric decontamination with activated charcoal should be administered just prior to N-acetylcysteine (NAC) to decrease systemic absorption if acetaminophen ingestion is known or suspected to have occurred within a few hours of presentation. Serum acetaminophen levels should be obtained immediately if the patient presents 4 hours or more after ingestion to assess potential risk of hepatotoxicity; acetaminophen levels drawn less than 4 hours post-ingestion may be misleading. To obtain the best possible outcome, NAC should be administered as soon as possible where impending or evolving liver injury is suspected. Intravenous NAC may be administered when circumstances preclude oral administration.

Vigorous supportive therapy is required in severe intoxication. Procedures to limit the continuing absorption of the drug must be readily performed since the hepatic injury is dose dependent and occurs early in the course of intoxication.

Important Dosage and Administration Instructions
Use the lowest effective dosage for the shortest duration consistent with individual patient treatment goals [see WARNINGS].
Initiate the dosing regimen for each patient individually, taking into account the patient's severity of pain, patient response, prior analgesic treatment experience, and risk factors for addiction, abuse, and misuse [see WARNINGS].
Follow patients closely for respiratory depression, especially within the first 24-72 hours of initiating therapy and following dosage increases with hydrocodone bitartrate and acetaminophen tablets and adjust the dosage accordingly [see WARNINGS].
Patient Access to Naloxone for the Emergency Treatment of Opioid Overdose
Discuss the availability of naloxone for the emergency treatment of opioid overdose with the patient and caregiver and assess the potential need for access to naloxone, both when initiating and renewing treatment with hydrocodone bitartrate and acetaminophen tablets [see WARNINGS, Life-Threatening Respiratory Depression; PRECAUTIONS, Information for Patients/Caregivers].
Inform patients and caregivers about the various ways to obtain naloxone as permitted by individual state naloxone dispensing and prescribing regulations (e.g., by prescription, directly from a pharmacist, or as part of a community-based program).
Consider prescribing naloxone, based on the patients risk factors for overdose, such as concomitant use of CNS depressants, a history of opioid use disorder, or prior opioid overdose. The presence of risk factors for overdose should not prevent the proper management of pain in any given patient [see WARNINGS, Addiction, Abuse, and Misuse, Life-Threatening Respiratory Depression, Risks from Concomitant Use with Benzodiazepines or Other CNS Depressants].
Consider prescribing naloxone when the patient has household members (including children) or other close contacts at risk for accidental ingestion or overdose.
Initial Dosage
Initiating Treatment with Hydrocodone Bitartrate and Acetaminophen Tablets
2.5 mg/325 mg The usual adult dosage is one or two tablets every four to six hours as needed for pain. The total daily dosage should not exceed 8 tablets.
5 mg/325 mg The usual adult dosage is one or two tablets every four to six hours as needed for pain. The total daily dosage should not exceed 8 tablets.
7.5 mg/325 mg,
10 mg/325 mg
The usual adult dosage is one tablet every four to six hours as needed for pain. The total daily dosage should not exceed 6 tablets.
Conversion from Other Opioids to Hydrocodone Bitartrate and Acetaminophen Tablets
There is inter-patient variability in the potency of opioid drugs and opioid formulations. Therefore, a conservative approach is advised when determining the total daily dosage of hydrocodone bitartrate and acetaminophen tablets. It is safer to underestimate a patient’s 24-hour hydrocodone bitartrate and acetaminophen tablets dosage than to overestimate the 24-hour hydrocodone bitartrate and acetaminophen tablets dosage and manage an adverse reaction due to overdose.
Conversion from Hydrocodone Bitartrate and Acetaminophen Tablets to Extended-Release Hydrocodone
The relative bioavailability of hydrocodone from hydrocodone bitartrate and acetaminophen tablets compared to extended-release hydrocodone products is unknown, so conversion to extended-release products must be accompanied by close observation for signs of excessive sedation and respiratory depression.
Titration and Maintenance of Therapy
Individually titrate hydrocodone bitartrate and acetaminophen tablets to a dose that provides adequate analgesia and minimizes adverse reactions. Continually reevaluate patients receiving hydrocodone bitartrate and acetaminophen tablets to assess the maintenance of pain control and the relative incidence of adverse reactions, as well as monitoring for the development of addiction, abuse, or misuse [see WARNINGS]. Frequent communication is important among the prescriber, other members of the healthcare team, the patient, and the caregiver/family during periods of changing analgesic requirements, including initial titration.
If the level of pain increases after dosage stabilization, attempt to identify the source of increased pain before increasing the hydrocodone bitartrate and acetaminophen tablets dosage. If unacceptable opioid-related adverse reactions are observed, consider reducing the dosage. Adjust the dosage to obtain an appropriate balance between management of pain and opioid-related adverse reactions.
Safe Reduction or Discontinuation of Hydrocodone Bitartrate and Acetaminophen Tablets
Do not abruptly discontinue hydrocodone bitartrate and acetaminophen tablets in patients who may be physically dependent on opioids. Rapid discontinuation of opioid analgesics in patients who are physically dependent on opioids has resulted in serious withdrawal symptoms, uncontrolled pain, and suicide. Rapid discontinuation has also been associated with attempts to find other sources of opioid analgesics, which may be confused with drug-seeking for abuse. Patients may also attempt to treat their pain or withdrawal symptoms with illicit opioids, such as heroin, and other substances.
When a decision has been made to decrease the dose or discontinue therapy in an opioid-dependent patient taking hydrocodone bitartrate and acetaminophen tablets, there are a variety of factors that should be considered, including the dose of hydrocodone bitartrate and acetaminophen tablets the patient has been taking, the duration of treatment, the type of pain being treated, and the physical and psychological attributes of the patient. It is important to ensure ongoing care of the patient and to agree on an appropriate tapering schedule and follow-up plan so that patient and provider goals and expectations are clear and realistic. When opioid analgesics are being discontinued due to a suspected substance use disorder, evaluate and treat the patient, or refer for evaluation and treatment of the substance use disorder. Treatment should include evidence-based approaches, such as medication assisted treatment of opioid use disorder. Complex patients with co-morbid pain and substance use disorders may benefit from referral to a specialist.
There are no standard opioid tapering schedules that are suitable for all patients. Good clinical practice dictates a patient-specific plan to taper the dose of the opioid gradually. For patients on hydrocodone bitartrate and acetaminophen tablets who are physically opioid-dependent, initiate the taper by a small enough increment (e.g., no greater than 10% to 25% of the total daily dose) to avoid withdrawal symptoms, and proceed with dose-lowering at an interval of every 2 to 4 weeks. Patients who have been taking opioids for briefer periods of time may tolerate a more rapid taper.
It may be necessary to provide the patient with lower dosage strengths to accomplish a successful taper. Reassess the patient frequently to manage pain and withdrawal symptoms, should they emerge. Common withdrawal symptoms include restlessness, lacrimation, rhinorrhea, yawning, perspiration, chills, myalgia, and mydriasis. Other signs and symptoms also may develop, including irritability, anxiety, backache, joint pain, weakness, abdominal cramps, insomnia, nausea, anorexia, vomiting, diarrhea, or increased blood pressure, respiratory rate, or heart rate. If withdrawal symptoms arise, it may be necessary to pause the taper for a period of time or raise the dose of the opioid analgesic to the previous dose, and then proceed with a slower taper. In addition, monitor patients for any changes in mood, emergence of suicidal thoughts, or use of other substances.
When managing patients taking opioid analgesics, particularly those who have been treated for a long duration and/or with high doses for chronic pain, ensure that a multimodal approach to pain management, including mental health support (if needed), is in place prior to initiating an opioid analgesic taper. A multimodal approach to pain management may optimize the treatment of chronic pain, as well as assist with the successful tapering of the opioid analgesic [see WARNINGS/ Withdrawal, DRUG ABUSE AND DEPENDENCE].

HOW SUPPLIED

Hydrocodone Bitartrate and Acetaminophen Tablets, USP are supplied as

5 mg/325 mg

containing 5 mg hydrocodone bitartrate and 325 mg acetaminophen. Off white/white capsule shaped tablet debossed ‘T 257’ on one side and plain on other side with bisect line.

Bottles of 100 Tablets

Bottles of 500 Tablets

10 mg/325 mg

containing 10 mg hydrocodone bitartrate and 325 mg acetaminophen. Off white/white capsule shaped tablet debossed ‘T 259’ on one side and plain on other side with bisect line.

Bottles of 100 Tablets

Bottles of 500 Tablets

Store at 20° to 25°C (68° to 77°F) [see USP Controlled Room Temperature].

Dispense in a tight, light-resistant container as defined in the USP with a child-resistant closure.

Store hydrocodone bitartrate and acetaminophen tablets securely and dispose of properly [see PRECAUTIONS/Information for Patients].

Manufactured by:

Ascent Pharmaceuticals, Inc.

Central Islip, NY 11722

Manufactured for:

Camber Pharmaceuticals, Inc.

Piscataway, NJ 08854

Revised: 05/21

MEDICATION GUIDE

LABEL RSS
SHAREBOOKMARK & SHARE
VIEW PACKAGE PHOTOS
Package PhotoPackage Photo
SAFETY
Boxed Warnings
Report Adverse Events
FDA Safety Recalls
Presence in Breast Milk
RELATED RESOURCES
Medline Plus
Clinical Trials
PubMed
Biochemical Data Summary
MORE INFO FOR THIS DRUG
View Labeling Archives
RxNorm
Get Label RSS Feed
View NDC Code(s)NEW!
NDC Code(s): 31722-996-01, 31722-996-05, 31722-997-01, 31722-997-05
Packager: Camber Pharmaceuticals, Inc.
Category: HUMAN PRESCRIPTION DRUG LABEL
DEA Schedule: CII
Marketing Status: Abbreviated New Drug Application
DRUG LABEL INFORMATIONUpdated May 21, 2021
If you are a consumer or patient please visit this version.
DOWNLOAD DRUG LABEL INFO: PDF XMLMEDICATION GUIDE: HTML
OFFICIAL LABEL (PRINTER FRIENDLY)
VIEW ALL SECTIONS
BOXED WARNING (WHAT IS THIS?)
WARNING: ADDICTION, ABUSE, AND MISUSE; RISK EVALUATION AND MITIGATION STRATEGY (REMS); LIFE-THREATENING RESPIRATORY DEPRESSION; ACCIDENTAL INGESTION; NEONATAL OPIOID WITHDRAWAL SYNDROME; CYTOCHROME P450 3A4 INTERACTION; HEPATOTOXICITY; and RISKS FROM CONCOMITANT USE WITH BENZODIAZEPINES OR OTHER CNS DEPRESSANTS
Addiction, Abuse, and Misuse: RISK EVALUATION AND MITIGATION STRATEGY (REMS)
Hydrocodone bitartrate and acetaminophen tablets expose patients and other users to the risks of opioid addiction, abuse, and misuse, which can lead to overdose and death. Assess each patient’s risk prior to prescribing hydrocodone bitartrate and acetaminophen tablets, and monitor all patients regularly for the development of these behaviors and conditions [see WARNINGS].
Opioid Analgesic Risk Evaluation and Mitigation Strategy (REMS):
To ensure that the benefits of opioid analgesics outweigh the risks of addiction, abuse, and misuse, the Food and Drug Administration (FDA) has required a REMS for these products [see WARNINGS]. Under the requirements of the REMS, drug companies with approved opioid analgesic products must make REMS-compliant education programs available to healthcare providers. Healthcare providers are strongly encouraged to
complete a REMS-compliant education program,
counsel patients and/or their caregivers, with every prescription, on safe use, serious risks, storage, and disposal of these products,
emphasize to patients and their caregivers the importance of reading the Medication Guide every time it is provided by their pharmacist, and
consider other tools to improve patient, household, and community safety.
Life-Threatening Respiratory Depression
Serious, life-threatening, or fatal respiratory depression may occur with use of hydrocodone bitartrate and acetaminophen tablets. Monitor for respiratory depression especially during initiation of hydrocodone bitartrate and acetaminophen tablets or following a dose increase [see WARNINGS].
Accidental Ingestion
Accidental ingestion of hydrocodone bitartrate and acetaminophen tablets, especially by children, can result in a fatal overdose of hydrocodone bitartrate and acetaminophen tablets [see WARNINGS].
Neonatal Opioid Withdrawal Syndrome
Prolonged use of hydrocodone bitartrate and acetaminophen tablets during pregnancy can result in neonatal opioid withdrawal syndrome, which may be life-threatening if not recognized and treated, and requires management according to protocols developed by neonatology experts. If opioid use is required for a prolonged period in a pregnant woman, advise the patient of the risk of neonatal opioid withdrawal syndrome and ensure that appropriate treatment will be available [see WARNINGS].
Cytochrome P450 3A4 Interaction
The concomitant use of hydrocodone bitartrate and acetaminophen tablets with all cytochrome P450 3A4 inhibitors may result in an increase in hydrocodone plasma concentrations, which could increase or prolong adverse reactions and may cause potentially fatal respiratory depression. In addition, discontinuation of a concomitantly used cytochrome P450 3A4 inducer may result in an increase in hydrocodone plasma concentrations. Monitor patients receiving hydrocodone bitartrate and acetaminophen tablets and any cytochrome P450 3A4 inhibitor or inducer for signs of respiratory depression or sedation [see CLINICAL PHARMACOLOGY, WARNINGS, PRECAUTIONS; Drug Interactions].
Hepatotoxicity
Acetaminophen has been associated with cases of acute liver failure, at times resulting in liver transplant and death. Most of the cases of liver injury are associated with the use of acetaminophen at doses that exceed 4,000 milligrams per day, and often involve more than one acetaminophen-containing product [see WARNINGS, OVERDOSAGE].
Risks from Concomitant Use with Benzodiazepines or Other CNS Depressants
Concomitant use of opioids with benzodiazepines or other central nervous system (CNS) depressants, including alcohol, may result in profound sedation, respiratory depression, coma, and death [see WARNINGS, PRECAUTIONS; Drug Interactions].
Reserve concomitant prescribing of hydrocodone bitartrate and acetaminophen tablets and benzodiazepines or other CNS depressants for use in patients for whom alternative treatment options are inadequate.
Limit dosages and durations to the minimum required.
Follow patients for signs and symptoms of respiratory depression and sedation.
CLOSE
DESCRIPTION
Hydrocodone bitartrate and acetaminophen, USP is available in tablet form for oral administration.
Hydrocodone bitartrate is an opioid analgesic and occurs as fine, white crystals or as a crystalline powder. It is affected by light. The chemical name is 4,5α-epoxy-3-methoxy-17-methylmorphinan-6-one tartrate (1:1) hydrate (2:5). It has the following structural formula:
Hydrocodone Bitartrate- Struct
Acetaminophen, 4' -hydroxyacetanilide, a slightly bitter, white, odorless, crystalline powder, is a non-opiate, non-salicylate analgesic and antipyretic. It has the following structural formula:
Acetaminophen- Struct
Each Hydrocodone Bitartrate and Acetaminophen Tablet, USP contains:
Strength Hydrocodone Bitartrate Acetaminophen
5 mg/325 mg 5 mg 325 mg
10 mg/325 mg 10 mg 325 mg
In addition, each tablet contains the following inactive ingredients: microcrystalline cellulose, corn starch, colloidal silicon dioxide, crospovidone, pregelatinized starch, povidone, and stearic acid.
Hydrocodone Bitartrate and Acetaminophen Tablets, USP complies to USP Dissolution Test 1.
CLOSE
CLINICAL PHARMACOLOGY
Mechanism of Action
Hydrocodone is a full opioid agonist with relative selectivity for the mu-opioid (μ) receptor, although it can interact with other opioid receptors at higher doses. The principal therapeutic action of hydrocodone is analgesia. Like all full opioid agonists, there is no ceiling effect for analgesia with hydrocodone. Clinically, dosage is titrated to provide adequate analgesia and may be limited by adverse reactions, including respiratory and CNS depression.
The precise mechanism of the analgesic action is unknown. However, specific CNS opioid receptors for endogenous compounds with opioid-like activity have been identified throughout the brain and spinal cord and are thought to play a role in the analgesic effects of this drug. The precise mechanism of the analgesic properties of acetaminophen is not established but is thought to involve central actions.
Pharmacodynamics
Effects on the Central Nervous System
The principal therapeutic action of hydrocodone is analgesia. Hydrocodone produces respiratory depression by direct action on brain stem respiratory centers. The respiratory depression involves a reduction in the responsiveness of the brain stem respiratory centers to both increases in carbon dioxide tension and electrical stimulation.
Hydrocodone causes miosis, even in total darkness. Pinpoint pupils are a sign of opioid overdose but are not pathognomonic (e.g., pontine lesions of hemorrhagic or ischemic origins may produce similar findings). Marked mydriasis rather than miosis may be seen due to hypoxia in overdose situations.
Therapeutic doses of acetaminophen have negligible effects on the cardiovascular or respiratory systems; however, toxic doses may cause circulatory failure and rapid, shallow breathing.
Effects on the Gastrointestinal Tract and Other Smooth Muscle
Hydrocodone causes a reduction in motility associated with an increase in smooth muscle tone in the antrum of the stomach and duodenum. Digestion of food in the small intestine is delayed and propulsive contractions are decreased. Propulsive peristaltic waves in the colon are decreased, while tone may be increased to the point of spasm, resulting in constipation. Other opioid-induced effects may include a reduction in biliary and pancreatic secretions, spasm of sphincter of Oddi, and transient elevations in serum amylase.
Effects on the Cardiovascular System
Hydrocodone produces peripheral vasodilation which may result in orthostatic hypotension or syncope. Manifestations of histamine release and/or peripheral vasodilation may include pruritus, flushing, red eyes, sweating, and/or orthostatic hypotension.
Effects on the Endocrine System
Opioids inhibit the secretion of adrenocorticotropic hormone (ACTH), cortisol, and luteinizing hormone (LH) in humans [see ADVERSE REACTIONS]. They also stimulate prolactin, growth hormone (GH) secretion, and pancreatic secretion of insulin and glucagon.
Chronic use of opioids may influence the hypothalamic-pituitary-gonadal axis, leading to androgen deficiency that may manifest as symptoms as low libido, impotence, erectile dysfunction, amenorrhea, or infertility. The causal role of opioids in the syndrome of hypogonadism is unknown because the various medical, physical, lifestyle, and psychological stressors that may influence gonadal hormone levels have not been adequately controlled for in studies conducted to date [see ADVERSE REACTIONS].
Effects on the Immune System
Opioids have been shown to have a variety of effects on components of the immune system. The clinical significance of these findings is unknown. Overall, the effects of opioids appear to be modestly immunosuppressive.
Concentration-Efficacy Relationships
The minimum effective analgesic concentration will vary widely among patients, especially among patients who have been previously treated with potent agonist opioids. The minimum effective analgesic concentration of hydrocodone for any individual patient may increase over time due to an increase in pain, the development of a new pain syndrome, and/or the development of analgesic tolerance [see DOSAGE AND ADMINISTRATION].
Concentration-Adverse Reaction Relationships
There is a relationship between increasing hydrocodone plasma concentration and increasing frequency of dose-related opioid adverse reactions such as nausea, vomiting, CNS effects, and respiratory depression. In opioid-tolerant patients, the situation may be altered by the development of tolerance to opioid-related adverse reactions [see DOSAGE AND ADMINISTRATION].
Pharmacokinetics
The behavior of the individual components is described below.
Hydrocodone
Following a 10 mg oral dose of hydrocodone administered to five adult male subjects, the mean peak concentration was 23.6 ± 5.2 ng/mL. Maximum serum levels were achieved at 1.3 ± 0.3 hours and the half-life was determined to be 3.8 ± 0.3 hours.
Hydrocodone exhibits a complex pattern of metabolism including O-demethylation, N-demethylation and 6-keto reduction to the corresponding 6-α- and 6-β-hydroxymetabolites. See OVERDOSAGE for toxicity information.
CYP3A4 mediated N-demethylation to norhydrocodone is the primary metabolic pathway of hydrocodone with a lower contribution from CYP2D6 mediated O-demethylation to hydromorphone. Hydromorphone is formed from the O-demethylation of hydrocodone and may contribute to the total analgesic effect of hydrocodone. Therefore, the formation of these and related metabolites can, in theory, be affected by other drugs [see PRECAUTIONS; Drug Interactions]. N-demethylation of hydrocodone to form norhydrocodone via CYP3A4 while O-demethylation of hydrocodone to hydromorphone is predominantly catalyzed by CYP2D6 and to a lesser extent by an unknown low affinity CYP enzyme. Hydrocodone and its metabolites are eliminated primarily in the kidneys.
Acetaminophen
Acetaminophen is rapidly absorbed from the gastrointestinal tract and is distributed throughout most body tissues. A small fraction (10-25%) of acetaminophen is bound to plasma proteins. The plasma half-life is 1.25 to 3 hours, but may be increased by liver damage and following overdosage. Elimination of acetaminophen is principally by liver metabolism (conjugation) and subsequent renal excretion of metabolites. Acetaminophen is primarily metabolized in the liver by first-order kinetics and involves three principal separate pathways: conjugation with glucuronide; conjugation with sulfate; and oxidation via the cytochrome, P450-dependent, mixed-function oxidase enzyme pathway to form a reactive intermediate metabolite, which conjugates with glutathione and is then further metabolized to form cysteine and mercapturic acid conjugates. The principal cytochrome P450 isoenzyme involved appears to be CYP2E1, with CYP1A2 and CYP3A4 as additional pathways. Approximately 85% of an oral dose appears in the urine within 24 hours of administration, most as the glucuronide conjugate, with small amounts of other conjugates and unchanged drug.
See OVERDOSAGE for toxicity information.
CLOSE
INDICATIONS AND USAGE
Hydrocodone bitartrate and acetaminophen tablets, USP are indicated for the management of pain severe enough to require an opioid analgesic and for which alternative treatments are inadequate.
Limitations of Use
Because of the risks of addiction, abuse, and misuse, with opioids, even at recommended doses [see WARNINGS], reserve hydrocodone bitartrate and acetaminophen tablets, USP for use in patients for whom alternative treatment options (e.g., non-opioid analgesics):
have not been tolerated, or are not expected to be tolerated,
have not provided adequate analgesia, or are not expected to provide adequate analgesia
CLOSE
CONTRAINDICATIONS
Hydrocodone bitartrate and acetaminophen tablets are contraindicated in patients with: Significant respiratory depression [see WARNINGS] Acute or severe bronchial asthma in an unmonitored setting ...
WARNINGS
Addiction, Abuse, and Misuse - Hydrocodone bitartrate and acetaminophen tablets contain hydrocodone, a Schedule II controlled substance. As an opioid, hydrocodone bitartrate and acetaminophen ...
PRECAUTIONS
Risks of Driving and Operating Machinery - Hydrocodone bitartrate and acetaminophen tablets may impair the mental or physical abilities needed to perform potentially hazardous activities such as ...
ADVERSE REACTIONS
The following adverse reactions have been identified during post approval use of hydrocodone and acetaminophen tablets. Because these reactions are reported voluntarily from a population of uncertain size, it is not always possible to reliably estimate their frequency or establish a causal relationship to drug exposure.
The most frequently reported adverse reactions are light-headedness, dizziness, sedation, nausea and vomiting.
Other adverse reactions include:
Central Nervous System: Drowsiness, mental clouding, lethargy, impairment of mental and physical performance, anxiety, fear, dysphoria, psychological dependence, mood changes.
Gastrointestinal System: Constipation.
Genitourinary System: Ureteral spasm, spasm of vesical sphincters, and urinary retention.
Special Senses: Cases of hearing impairment or permanent loss have been reported predominately in patients with chronic overdose.
Dermatological: Skin rash, pruritus, Stevens-Johnson syndrome, toxic epidermal necrolysis, allergic reactions.
Hematological: Thrombocytopenia, agranulocytosis.
Serotonin syndrome: Cases of serotonin syndrome, a potentially life-threatening condition, have been reported during concomitant use of opioids with serotonergic drugs.
Adrenal insufficiency: Cases of adrenal insufficiency have been reported with opioid use, more often following greater than one month of use.
Anaphylaxis: Anaphylaxis has been reported with ingredients contained in hydrocodone bitartrate and acetaminophen tablets.
Androgen deficiency: Cases of androgen deficiency have occurred with chronic use of opioids [see CLINICAL PHARMACOLOGY].
CLOSE
DRUG ABUSE AND DEPENDENCE
Controlled Substance
Hydrocodone bitartrate and acetaminophen tablets contain hydrocodone, a Schedule II controlled substance.
Abuse
Hydrocodone bitartrate and acetaminophen tablets contain hydrocodone, a substance with a high potential for abuse similar to other opioids, including fentanyl, hydrocodone, hydromorphone, methadone, morphine, oxycodone, oxymorphone, and tapentadol, can be abused and are subject to misuse, addiction, and criminal diversion [see WARNINGS].
All patients treated with opioids require careful monitoring for signs of abuse and addiction, because use of opioid analgesic products carries the risk of addiction even under appropriate medical use.
Prescription drug abuse is the intentional non-therapeutic use of a prescription drug, even once, for its rewarding psychological or physiological effects.
Drug addiction is a cluster of behavioral, cognitive, and physiological phenomena that develop after repeated substance use and includes a strong desire to take the drug, difficulties in controlling its use, persisting in its use despite harmful consequences, a higher priority given to drug use than to other activities and obligations, increased tolerance, and sometimes a physical withdrawal.
“Drug-seeking” behavior is very common in persons with substance use disorders. Drug-seeking tactics include emergency calls or visits near the end of office hours, refusal to undergo appropriate examination, testing, or referral, repeated “loss” of prescriptions, tampering with prescriptions and reluctance to provide prior medical records or contact information for other treating healthcare provider(s). “Doctor shopping” (visiting multiple prescribers to obtain additional prescriptions) is common among drug abusers and people suffering from untreated addiction. Preoccupation with achieving adequate pain relief can be appropriate behavior in a patient with poor pain control.
Abuse and addiction are separate and distinct from physical dependence and tolerance. Healthcare providers should be aware that addiction may not be accompanied by concurrent tolerance and symptoms of physical dependence in all addicts. In addition, abuse of opioids can occur in the absence of true addiction.
Hydrocodone bitartrate and acetaminophen tablets, like other opioids, can be diverted for non-medical use into illicit channels of distribution. Careful record-keeping of prescribing information, including quantity, frequency, and renewal requests, as required by state and federal law, is strongly advised.
Proper assessment of the patient, proper prescribing practices, periodic re-evaluation of therapy, and proper dispensing and storage are appropriate measures that help to limit abuse of opioid drugs.
Risks Specific to Abuse of Hydrocodone Bitartrate and Acetaminophen Tablets
Hydrocodone bitartrate and acetaminophen tablets are for oral use only. Hydrocodone bitartrate and acetaminophen tablets pose a risk of overdose and death. The risk is increased with concurrent abuse of hydrocodone bitartrate and acetaminophen tablets with alcohol and other central nervous system depressants.
Parenteral drug abuse is commonly associated with transmission of infectious diseases such as hepatitis and HIV.
Dependence
Both tolerance and physical dependence can develop during chronic opioid therapy. Tolerance is the need for increasing doses of opioids to maintain a defined effect such as analgesia (in the absence of disease progression or other external factors). Tolerance may occur to both the desired and undesired effects of drugs, and may develop at different rates for different effects.
Physical dependence is a physiological state in which the body adapts to the drug after a period of regular exposure, resulting in withdrawal symptoms after abrupt discontinuation or a significant dosage reduction of a drug. Withdrawal also may be precipitated through the administration of drugs with opioid antagonist activity (e.g., naloxone, nalmefene), mixed agonist/antagonist analgesics (e.g., pentazocine, butorphanol, nalbuphine), or partial agonists (e.g., buprenorphine). Physical dependence may not occur to a clinically significant degree until after several days to weeks of continued opioid usage.
Do not abruptly discontinue hydrocodone bitartrate and acetaminophen tablets in a patient physically dependent on opioids. Rapid tapering of hydrocodone bitartrate and acetaminophen tablets in a patient physically dependent on opioids may lead to serious withdrawal symptoms, uncontrolled pain, and suicide. Rapid discontinuation has also been associated with attempts to find other sources of opioid analgesics, which may be confused with drug-seeking for abuse.
When discontinuing hydrocodone bitartrate and acetaminophen tablets, gradually taper the dosage using a patient specific plan that considers the following: the dose of hydrocodone bitartrate and acetaminophen tablets the patient has been taking, the duration of treatment, and the physical and psychological attributes of the patient. To improve the likelihood of a successful taper and minimize withdrawal symptoms, it is important that the opioid tapering schedule is agreed upon by the patient. In patients taking opioids for a long duration at high doses, ensure that a multimodal approach to pain management, including mental health support (if needed), is in place prior to initiating an opioid analgesic taper [see DOSAGE AND ADMINISTRATION, WARNINGS].
Infants born to mothers physically dependent on opioids will also be physically dependent and may exhibit respiratory difficulties and withdrawal signs [see PRECAUTIONS; Pregnancy].
CLOSE
OVERDOSAGE
Following an acute overdosage, toxicity may result from hydrocodone or acetaminophen.
Clinical Presentation
Acute overdosage with hydrocodone bitartrate and acetaminophen tablets can be manifested by respiratory depression, somnolence progressing to stupor or coma, skeletal muscle flaccidity, cold and clammy skin, constricted pupils, and, in some cases, pulmonary edema, bradycardia, hypotension, partial or complete airway obstruction, atypical snoring, and death. Marked mydriasis rather than miosis may be seen with hypoxia in overdose situations.
Acetaminophen
Dose-dependent, potentially fatal hepatic necrosis is the most serious adverse effect of acetaminophen overdosage. Renal tubular necrosis, hypoglycemic coma and coagulation defects may also occur.
Early symptoms following a potentially hepatotoxic overdose may include: nausea, vomiting, diaphoresis and general malaise. Clinical and laboratory evidence of hepatic toxicity may not be apparent until 48 to 72 hours post-ingestion.
Treatment of Overdose
Hydrocodone
In case of overdose, priorities are the re-establishment of a patent and protected airway and institution of assisted or controlled ventilation, if needed. Employ other supportive measures (including oxygen and vasopressors) in the management of circulatory shock and pulmonary edema as indicated. Cardiac arrest or arrhythmias will require advanced life-support techniques.
Opioid antagonists, such as naloxone, are specific antidotes to respiratory depression resulting from opioid overdose. For clinically significant respiratory or circulatory depression secondary to opioid overdose, administer an opioid antagonist.
Because the duration of opioid reversal is expected to be less than the duration of action of hydrocodone in hydrocodone bitartrate and acetaminophen tablets, carefully monitor the patient until spontaneous respiration is reliably reestablished. If the response to an opioid antagonist is suboptimal or only brief in nature, administer additional antagonist as directed by the product’s prescribing information.
In an individual physically dependent on opioids, administration of the recommended usual dosage of the antagonist will precipitate an acute withdrawal syndrome. The severity of the withdrawal symptoms experienced will depend on the degree of physical dependence and the dose of the antagonist administered. If a decision is made to treat serious respiratory depression in the physically dependent patient, administration of the antagonist should be initiated with care and by titration with smaller than usual doses of the antagonist.
Acetaminophen
Gastric decontamination with activated charcoal should be administered just prior to N-acetylcysteine (NAC) to decrease systemic absorption if acetaminophen ingestion is known or suspected to have occurred within a few hours of presentation. Serum acetaminophen levels should be obtained immediately if the patient presents 4 hours or more after ingestion to assess potential risk of hepatotoxicity; acetaminophen levels drawn less than 4 hours post-ingestion may be misleading. To obtain the best possible outcome, NAC should be administered as soon as possible where impending or evolving liver injury is suspected. Intravenous NAC may be administered when circumstances preclude oral administration.
Vigorous supportive therapy is required in severe intoxication. Procedures to limit the continuing absorption of the drug must be readily performed since the hepatic injury is dose dependent and occurs early in the course of intoxication.
CLOSE
DOSAGE AND ADMINISTRATION
Important Dosage and Administration Instructions
Use the lowest effective dosage for the shortest duration consistent with individual patient treatment goals [see WARNINGS].
Initiate the dosing regimen for each patient individually, taking into account the patient's severity of pain, patient response, prior analgesic treatment experience, and risk factors for addiction, abuse, and misuse [see WARNINGS].
Follow patients closely for respiratory depression, especially within the first 24-72 hours of initiating therapy and following dosage increases with hydrocodone bitartrate and acetaminophen tablets and adjust the dosage accordingly [see WARNINGS].
Patient Access to Naloxone for the Emergency Treatment of Opioid Overdose
Discuss the availability of naloxone for the emergency treatment of opioid overdose with the patient and caregiver and assess the potential need for access to naloxone, both when initiating and renewing treatment with hydrocodone bitartrate and acetaminophen tablets [see WARNINGS, Life-Threatening Respiratory Depression; PRECAUTIONS, Information for Patients/Caregivers].
Inform patients and caregivers about the various ways to obtain naloxone as permitted by individual state naloxone dispensing and prescribing regulations (e.g., by prescription, directly from a pharmacist, or as part of a community-based program).
Consider prescribing naloxone, based on the patients risk factors for overdose, such as concomitant use of CNS depressants, a history of opioid use disorder, or prior opioid overdose. The presence of risk factors for overdose should not prevent the proper management of pain in any given patient [see WARNINGS, Addiction, Abuse, and Misuse, Life-Threatening Respiratory Depression, Risks from Concomitant Use with Benzodiazepines or Other CNS Depressants].
Consider prescribing naloxone when the patient has household members (including children) or other close contacts at risk for accidental ingestion or overdose.
Initial Dosage
Initiating Treatment with Hydrocodone Bitartrate and Acetaminophen Tablets
2.5 mg/325 mg The usual adult dosage is one or two tablets every four to six hours as needed for pain. The total daily dosage should not exceed 8 tablets.
5 mg/325 mg The usual adult dosage is one or two tablets every four to six hours as needed for pain. The total daily dosage should not exceed 8 tablets.
7.5 mg/325 mg,
10 mg/325 mg
The usual adult dosage is one tablet every four to six hours as needed for pain. The total daily dosage should not exceed 6 tablets.
Conversion from Other Opioids to Hydrocodone Bitartrate and Acetaminophen Tablets
There is inter-patient variability in the potency of opioid drugs and opioid formulations. Therefore, a conservative approach is advised when determining the total daily dosage of hydrocodone bitartrate and acetaminophen tablets. It is safer to underestimate a patient’s 24-hour hydrocodone bitartrate and acetaminophen tablets dosage than to overestimate the 24-hour hydrocodone bitartrate and acetaminophen tablets dosage and manage an adverse reaction due to overdose.
Conversion from Hydrocodone Bitartrate and Acetaminophen Tablets to Extended-Release Hydrocodone
The relative bioavailability of hydrocodone from hydrocodone bitartrate and acetaminophen tablets compared to extended-release hydrocodone products is unknown, so conversion to extended-release products must be accompanied by close observation for signs of excessive sedation and respiratory depression.
Titration and Maintenance of Therapy
Individually titrate hydrocodone bitartrate and acetaminophen tablets to a dose that provides adequate analgesia and minimizes adverse reactions. Continually reevaluate patients receiving hydrocodone bitartrate and acetaminophen tablets to assess the maintenance of pain control and the relative incidence of adverse reactions, as well as monitoring for the development of addiction, abuse, or misuse [see WARNINGS]. Frequent communication is important among the prescriber, other members of the healthcare team, the patient, and the caregiver/family during periods of changing analgesic requirements, including initial titration.
If the level of pain increases after dosage stabilization, attempt to identify the source of increased pain before increasing the hydrocodone bitartrate and acetaminophen tablets dosage. If unacceptable opioid-related adverse reactions are observed, consider reducing the dosage. Adjust the dosage to obtain an appropriate balance between management of pain and opioid-related adverse reactions.
Safe Reduction or Discontinuation of Hydrocodone Bitartrate and Acetaminophen Tablets
Do not abruptly discontinue hydrocodone bitartrate and acetaminophen tablets in patients who may be physically dependent on opioids. Rapid discontinuation of opioid analgesics in patients who are physically dependent on opioids has resulted in serious withdrawal symptoms, uncontrolled pain, and suicide. Rapid discontinuation has also been associated with attempts to find other sources of opioid analgesics, which may be confused with drug-seeking for abuse. Patients may also attempt to treat their pain or withdrawal symptoms with illicit opioids, such as heroin, and other substances.
When a decision has been made to decrease the dose or discontinue therapy in an opioid-dependent patient taking hydrocodone bitartrate and acetaminophen tablets, there are a variety of factors that should be considered, including the dose of hydrocodone bitartrate and acetaminophen tablets the patient has been taking, the duration of treatment, the type of pain being treated, and the physical and psychological attributes of the patient. It is important to ensure ongoing care of the patient and to agree on an appropriate tapering schedule and follow-up plan so that patient and provider goals and expectations are clear and realistic. When opioid analgesics are being discontinued due to a suspected substance use disorder, evaluate and treat the patient, or refer for evaluation and treatment of the substance use disorder. Treatment should include evidence-based approaches, such as medication assisted treatment of opioid use disorder. Complex patients with co-morbid pain and substance use disorders may benefit from referral to a specialist.
There are no standard opioid tapering schedules that are suitable for all patients. Good clinical practice dictates a patient-specific plan to taper the dose of the opioid gradually. For patients on hydrocodone bitartrate and acetaminophen tablets who are physically opioid-dependent, initiate the taper by a small enough increment (e.g., no greater than 10% to 25% of the total daily dose) to avoid withdrawal symptoms, and proceed with dose-lowering at an interval of every 2 to 4 weeks. Patients who have been taking opioids for briefer periods of time may tolerate a more rapid taper.
It may be necessary to provide the patient with lower dosage strengths to accomplish a successful taper. Reassess the patient frequently to manage pain and withdrawal symptoms, should they emerge. Common withdrawal symptoms include restlessness, lacrimation, rhinorrhea, yawning, perspiration, chills, myalgia, and mydriasis. Other signs and symptoms also may develop, including irritability, anxiety, backache, joint pain, weakness, abdominal cramps, insomnia, nausea, anorexia, vomiting, diarrhea, or increased blood pressure, respiratory rate, or heart rate. If withdrawal symptoms arise, it may be necessary to pause the taper for a period of time or raise the dose of the opioid analgesic to the previous dose, and then proceed with a slower taper. In addition, monitor patients for any changes in mood, emergence of suicidal thoughts, or use of other substances.
When managing patients taking opioid analgesics, particularly those who have been treated for a long duration and/or with high doses for chronic pain, ensure that a multimodal approach to pain management, including mental health support (if needed), is in place prior to initiating an opioid analgesic taper. A multimodal approach to pain management may optimize the treatment of chronic pain, as well as assist with the successful tapering of the opioid analgesic [see WARNINGS/ Withdrawal, DRUG ABUSE AND DEPENDENCE].
CLOSE
HOW SUPPLIED
Hydrocodone Bitartrate and Acetaminophen Tablets, USP are supplied as
5 mg/325 mg
containing 5 mg hydrocodone bitartrate and 325 mg acetaminophen. Off white/white capsule shaped tablet debossed ‘T 257’ on one side and plain on other side with bisect line.
NDC 31722-996-01, Bottles of 100 Tablets
NDC 31722-996-05, Bottles of 500 Tablets
10 mg/325 mg
containing 10 mg hydrocodone bitartrate and 325 mg acetaminophen. Off white/white capsule shaped tablet debossed ‘T 259’ on one side and plain on other side with bisect line.
NDC 31722-997-01, Bottles of 100 Tablets
NDC 31722-997-05, Bottles of 500 Tablets
Store at 20° to 25°C (68° to 77°F) [see USP Controlled Room Temperature].
Dispense in a tight, light-resistant container as defined in the USP with a child-resistant closure.
Store hydrocodone bitartrate and acetaminophen tablets securely and dispose of properly [see PRECAUTIONS/Information for Patients].
Manufactured by:
Ascent Pharmaceuticals, Inc.
Central Islip, NY 11722
Manufactured for:
Camber Pharmaceuticals, Inc.
Piscataway, NJ 08854
Revised: 05/21
CLOSE
MEDICATION GUIDE
MEDICATION GUIDE
Hydrocodone Bitartrate (hye" droe koe' done bye tar’ trate) and Acetaminophen (a seet"a min' oh fen) Tablets USP, CII
Hydrocodone Bitartrate and Acetaminophen Tablets are:
A strong prescription pain medicine that contains an opioid (narcotic) that is used to manage pain severe enough to require an opioid pain medicine, when other pain treatments such as non-opioid pain medicines do not treat your pain well enough or you cannot tolerate them.
An opioid pain medicine that can put you at risk for overdose and death. Even if you take your dose correctly as prescribed you are at risk for opioid addiction, abuse, and misuse that can lead to death.
Important information about Hydrocodone Bitartrate and Acetaminophen Tablets:
Get emergency help or call 911 right away if you take too much Hydrocodone Bitartrate and Acetaminophen Tablets (overdose). When you first start taking Hydrocodone Bitartrate and Acetaminophen Tablets, when your dose is changed, or if you take too much (overdose), serious or life-threatening breathing problems that can lead to death may occur. Talk to your healthcare provider about naloxone, a medicine for the emergency treatment of an opioid overdose.
Taking Hydrocodone Bitartrate and Acetaminophen Tablets with other opioid medicines, benzodiazepines, alcohol, or other central nervous system depressants (including street drugs) can cause severe drowsiness, decreased awareness, breathing problems, coma, and death.
Never give anyone else your Hydrocodone Bitartrate and Acetaminophen Tablets. They could die from taking it. Selling or giving away Hydrocodone Bitartrate and Acetaminophen Tablets is against the law.
Store Hydrocodone Bitartrate and Acetaminophen Tablets securely, out of sight and reach of children, and in a location not accessible by others, including visitors to the home.
Do not take Hydrocodone Bitartrate and Acetaminophen Tablets if you have:
severe asthma, trouble breathing, or other lung problems.
a bowel blockage or have narrowing of the stomach or intestines.
known hypersensitivity to hydrocodone or acetaminophen, or any ingredient in Hydrocodone Bitartrate and Acetaminophen Tablets
Before taking Hydrocodone Bitartrate and Acetaminophen Tablets, tell your healthcare provider if you have a history of:
head injury, seizures
liver, kidney, thyroid problems
problems urinating
pancreas or gallbladder problems
abuse of street or prescription drugs, alcohol addiction, opioid overdose, or mental health problems.
Tell your healthcare provider if you are:
pregnant or planning to become pregnant. Prolonged use of Hydrocodone Bitartrate and Acetaminophen Tablets during pregnancy can cause withdrawal symptoms in your newborn baby that could be life-threatening if not recognized and treated.
breastfeeding. Hydrocodone bitartrate and acetaminophen passes into breast milk and may harm your baby.
living in a household where there are small children or someone who has abused street or prescription drugs.
taking prescription or over-the-counter medicines, vitamins, or herbal supplements. Taking Hydrocodone Bitartrate and Acetaminophen Tablets with certain other medicines can cause serious side effects that could lead to death.
When taking Hydrocodone Bitartrate and Acetaminophen Tablets:
Do not change your dose. Take Hydrocodone Bitartrate and Acetaminophen Tablets exactly as prescribed by your healthcare provider. Use the lowest dose possible for the shortest time needed.
Take your prescribed dose every four to six hours as needed for pain.
Do not take more than your prescribed dose. If you miss a dose, take your next dose at your usual time.
Call your healthcare provider if the dose you are taking does not control your pain.
If you have been taking Hydrocodone Bitartrate and Acetaminophen Tablets regularly, do not stop taking Hydrocodone Bitartrate and Acetaminophen Tablets without talking to your healthcare provider.
Dispose of expired, unwanted, or unused Hydrocodone Bitartrate and Acetaminophen Tablets by promptly flushing down the toilet, if a drug take-back option is not readily available. Visit www.fda.gov/drugdisposal for additional information on disposal of unused medicines.
While taking Hydrocodone Bitartrate and Acetaminophen Tablets DO NOT:
Drive or operate heavy machinery, until you know how Hydrocodone Bitartrate and Acetaminophen Tablets affect you. Hydrocodone Bitartrate and Acetaminophen Tablets can make you sleepy, dizzy, or lightheaded.
Drink alcohol or use prescription or over-the-counter medicines that contain alcohol. Using products containing alcohol during treatment with Hydrocodone Bitartrate and Acetaminophen Tablets may cause you to overdose and die.
The possible side effects of Hydrocodone Bitartrate and Acetaminophen Tablets:
constipation, nausea, sleepiness, vomiting, tiredness, headache, dizziness, abdominal pain. Call your healthcare provider if you have any of these symptoms and they are severe.
Get emergency medical help or call 911 right away if you have:
trouble breathing, shortness of breath, fast heartbeat, chest pain, swelling of your face, tongue, or throat, extreme drowsiness, light-headedness when changing positions, feeling faint, agitation, high body temperature, trouble walking, stiff muscles, or mental changes such as confusion.
These are not all the possible side effects of Hydrocodone Bitartrate and Acetaminophen Tablets. Call your doctor for medical advice about side effects. You may report side effects to Camber Pharmaceuticals Inc., at 1-866-495-8330 or to FDA at 1-800-FDA-1088. For more information go to dailymed.nlm.nih.gov
Manufactured by:
Ascent Pharmaceuticals, Inc.
Central Islip, NY 11722
Manufactured for:
Camber Pharmaceuticals, Inc.
Piscataway, NJ 08854
This Medication Guide has been approved by the U.S. Food and Drug Administration. Revised: 05/21